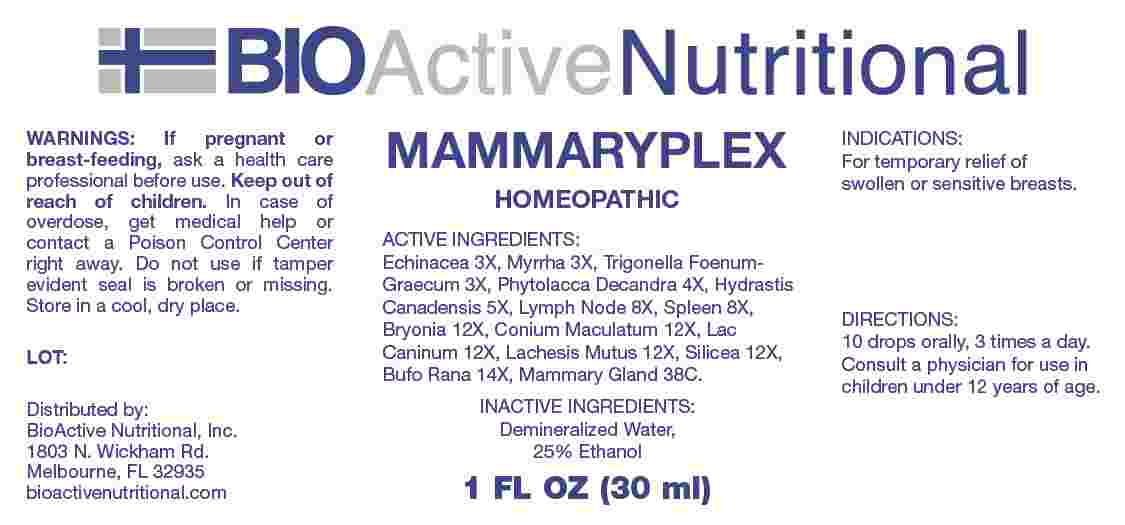 DRUG LABEL: Mammaryplex
NDC: 43857-0647 | Form: LIQUID
Manufacturer: BioActive Nutritional, Inc.
Category: homeopathic | Type: HUMAN OTC DRUG LABEL
Date: 20241115

ACTIVE INGREDIENTS: ECHINACEA ANGUSTIFOLIA WHOLE 3 [hp_X]/1 mL; MYRRH 3 [hp_X]/1 mL; FENUGREEK SEED 3 [hp_X]/1 mL; PHYTOLACCA AMERICANA ROOT 4 [hp_X]/1 mL; GOLDENSEAL 5 [hp_X]/1 mL; SUS SCROFA LYMPH 8 [hp_X]/1 mL; SUS SCROFA SPLEEN 8 [hp_X]/1 mL; BRYONIA ALBA ROOT 12 [hp_X]/1 mL; CONIUM MACULATUM FLOWERING TOP 12 [hp_X]/1 mL; CANIS LUPUS FAMILIARIS MILK 12 [hp_X]/1 mL; LACHESIS MUTA VENOM 12 [hp_X]/1 mL; SILICON DIOXIDE 12 [hp_X]/1 mL; BUFO BUFO CUTANEOUS GLAND 14 [hp_X]/1 mL; BOS TAURUS MAMMARY GLAND 38 [hp_C]/1 mL
INACTIVE INGREDIENTS: WATER; ALCOHOL

DRUG FACTS:

ACTIVE INGREDIENTS:

Echinacea 3X, Myrrha 3X, Trigonella Foenum-Graecum 3X, Phytolacca Decandra 4X, Hydrastis Canadensis 5X, Lymph Node 8X, Spleen 8X, Bryonia 12X, Conium Maculatum 12X, Lac Caninum 12X, Lachesis Mutus 12X, Silicea 12X, Bufo Rana 14X, Mammary Gland 38C.

PURPOSE:

For temporary relief of swollen or sensitive breasts.

WARNINGS:

If pregnant or breast-feeding, ask a health care professional before use.

Keep out of reach of children. In case of overdose, get medical help or contact a Poison Control Center right away.

Do not use if tamper evident seal is broken or missing.

Store in cool, dry place.

KEEP OUT OF REACH OF CHILDREN:

In case of overdose, get medical help or contact a Poison Control Center right away.

DIRECTIONS:

10 drops orally, 3 times a day. Consult a physician for use in children under 12 years of age.

INDICATIONS:

For temporary relief of swollen or sensitive breasts.

INACTIVE INGREDIENTS:

Demineralized Water, 25% Ethanol

QUESTIONS:

Distributed by:
BioActive Nutritional, Inc.
1803 N. Wickham Rd.
Melbourne, FL 32935
bioactivenutritional.com

PACKAGE LABEL DISPLAY:

BIOActiveNutritional

MAMMARYPLEX

HOMEOPATHIC

1 FL OZ (30 ml)